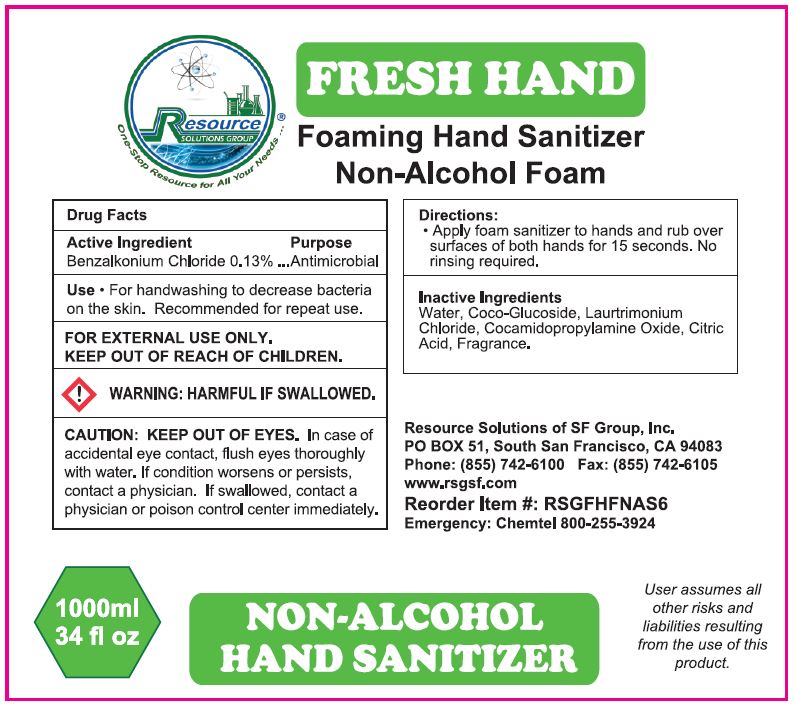 DRUG LABEL: FRESH HAND FOAMING HAND SANITIZER NON-ALCOHOL FOAM
NDC: 70415-204 | Form: SOLUTION
Manufacturer: CWGC LA Inc.
Category: otc | Type: HUMAN OTC DRUG LABEL
Date: 20230921

ACTIVE INGREDIENTS: BENZALKONIUM CHLORIDE 0.13 g/100 mL
INACTIVE INGREDIENTS: WATER; COCO GLUCOSIDE; LAURTRIMONIUM CHLORIDE; COCAMIDOPROPYLAMINE OXIDE; ANHYDROUS CITRIC ACID

CWGC (as PLD) - Resource Solutions Fresh Hand Foaming Hand Sanitizer Non-Alcohol Foam (70415-204)

Active ingredient

BENZALKONIUM CHLORIDE 0.13%

Purpose

Antibacterial

PURPOSE

ANTIMICROBIAL

Use

- FOR HANDWASHING TO DECREASE BACTERIA ON THE SKIN. RECOMMENDED FOR REPEATED USE.

WARNINGS

For external use only.

WARNING: HARMFUL IF SWALLOWED.

CAUTION: KEEP OUT OF EYES. IN CASE OF ACCIDENTAL EYE CONTACT, FLUSH EYES THOROUGHLY WITH WATER. IF CONDITION WORSENS OR PERSISTS, CONTACT A PHYSICIAN. IF SWALLOWED, CONTACT A PHYSICIAN OR POISON CONTROL CENTER IMMEDIATELY.

When using this product

- avoid contact with eyes. In case of eye contact, flush with water

Keep out of reach of children.

If swallowed, get medical help or contact a Poison Control Center right away.

Keep out of reach of children.

DIRECTIONS

- APPLY FOAM SANITIZER TO HANDS AND RUB OVER SURFACES OF BOTH HANDS FOR 15 SECONDS. NO RINSING REQUIRED.

Inactive ingredients

WATER, COCO-GLUCOSIDE, LAURTRIMONIUM CHLORIDE, COCAMIDOPROPYLAMINE OXIDE, CITRIC ACID, FRAGRANCE.